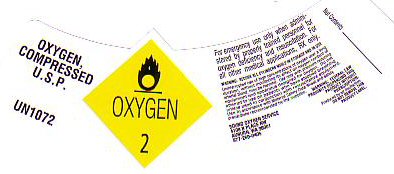 DRUG LABEL: OXYGEN
NDC: 43314-001 | Form: GAS
Manufacturer: Sound Oxygen Service, Inc.
Category: prescription | Type: HUMAN PRESCRIPTION DRUG LABEL
Date: 20100101

ACTIVE INGREDIENTS: OXYGEN 99 L/100 L

OXYGEN COMPRESSED LABEL

OXYGEN COMPRESSED U.S.P. UN 1072 OXYGEN-2

FOR EMERGENCY USE ONLY WHEN ADMINISTERED BY PROPERLY TRAINED PERSONNEL FOR OXYGEN DEFICIENCY AND RESUSCITATION. FOR ALL OTHER MEDICAL APPLICATIONS Rx ONLY.

NET CONTENTS:____________________________

PRODUCT WARNINGS AND PRECAUTIONS

WARNING: SECURE ALL CYLINDERS WHILE IN STORAGE AND IN USE. UNINTERRUPTED USE OF HIGH CONCENTRATIONS OF OXYGEN OVER A LONG DURATION WITHOUT MONITORING ITS EFFECT ON OXYGEN CONTENT OF ARTERIAL BLOOD MAY BE HARMFUL. USE ONLY WITH PRESSURE REDUCING EQUIPMENT AND APPARATUS DESIGNED FOR OXYGEN. DO NOT ATTEMPT TO USE ON PATIENTS WHO HAVE STOPPED BREATHING, UNLESS USED IN CONJUNCTION WITH RESUSCITATIVE EQUIPMENT. USE IN ACCORDANCE WITH MATERIAL SAFETY DATA SHEETS AND SAFETY PRECAUTIONS RECOMMENDED BY THE SUPPLIER.

WARNING: FEDERAL LAW PROHIBITS DISPENSING WITHOUT A PRESCRIPTION. PRODUCED BY AIR LIQUEFACTION. DO NOT REMOVE THIS PRODUCT LABEL.